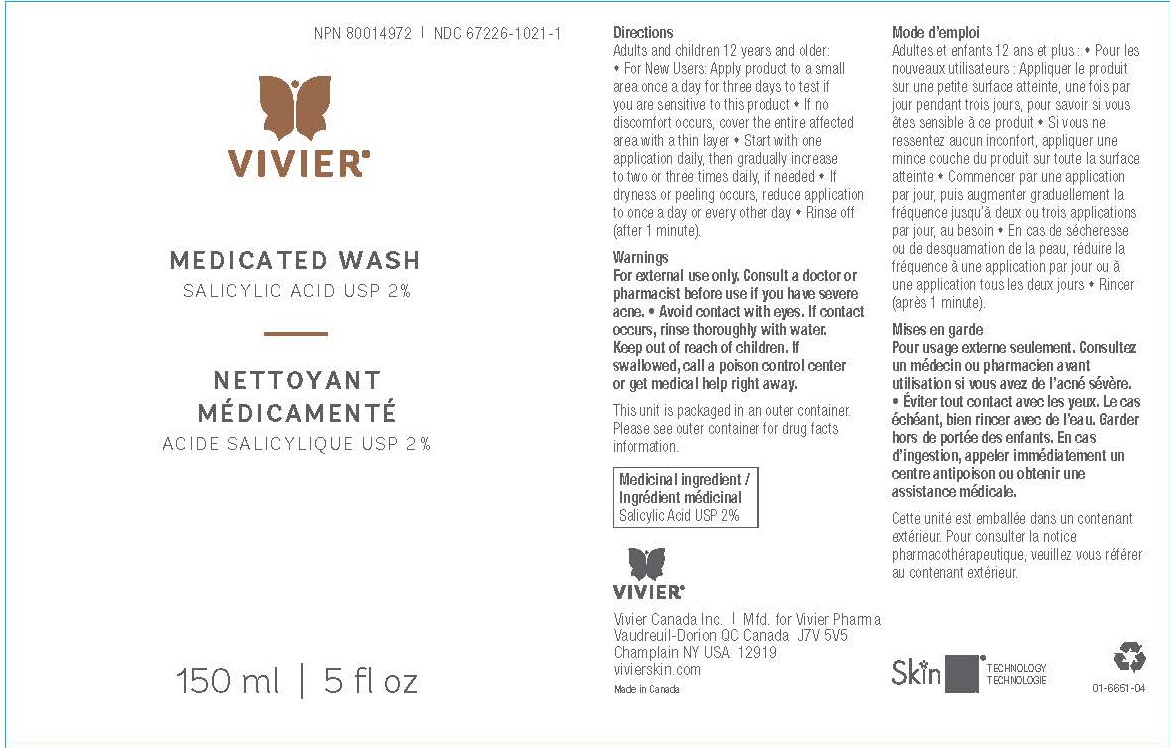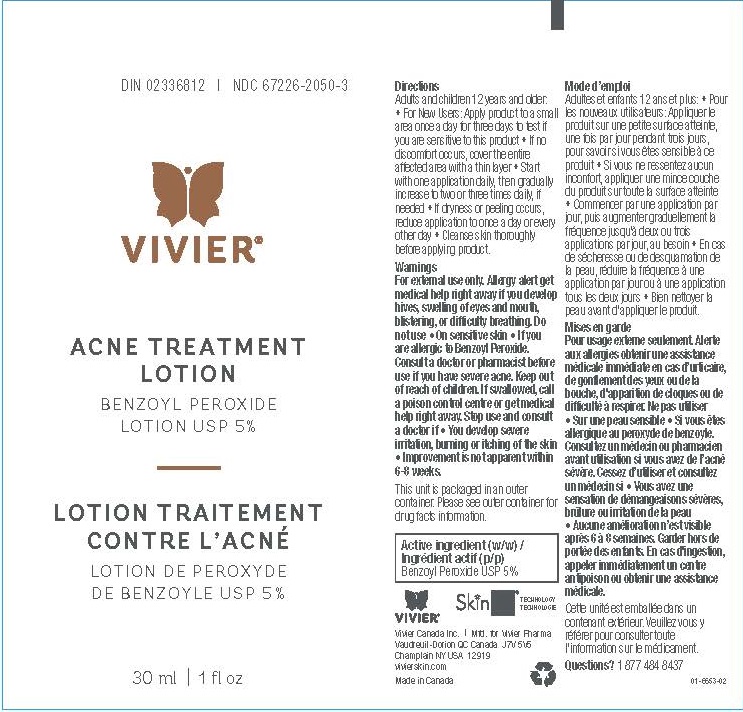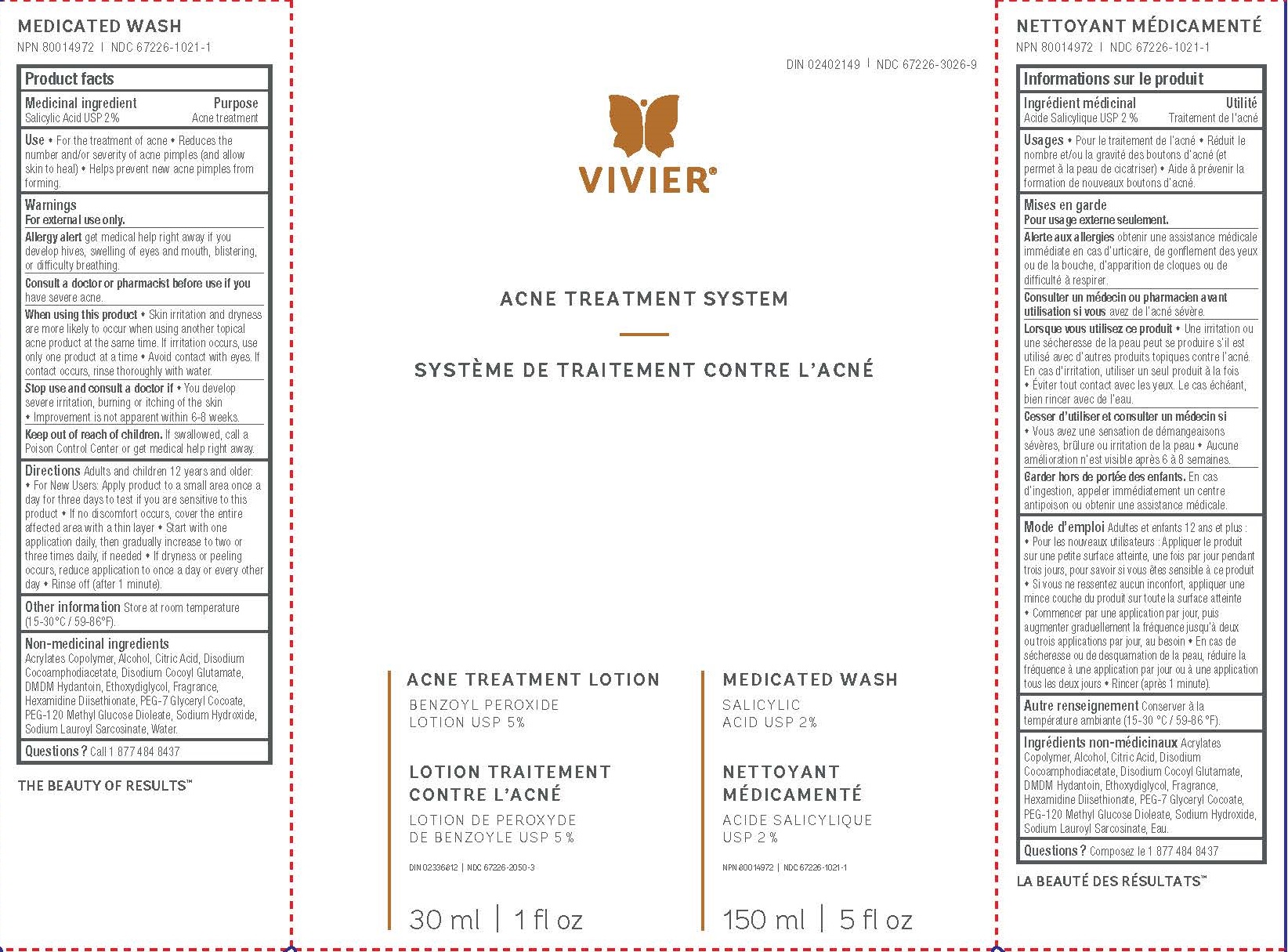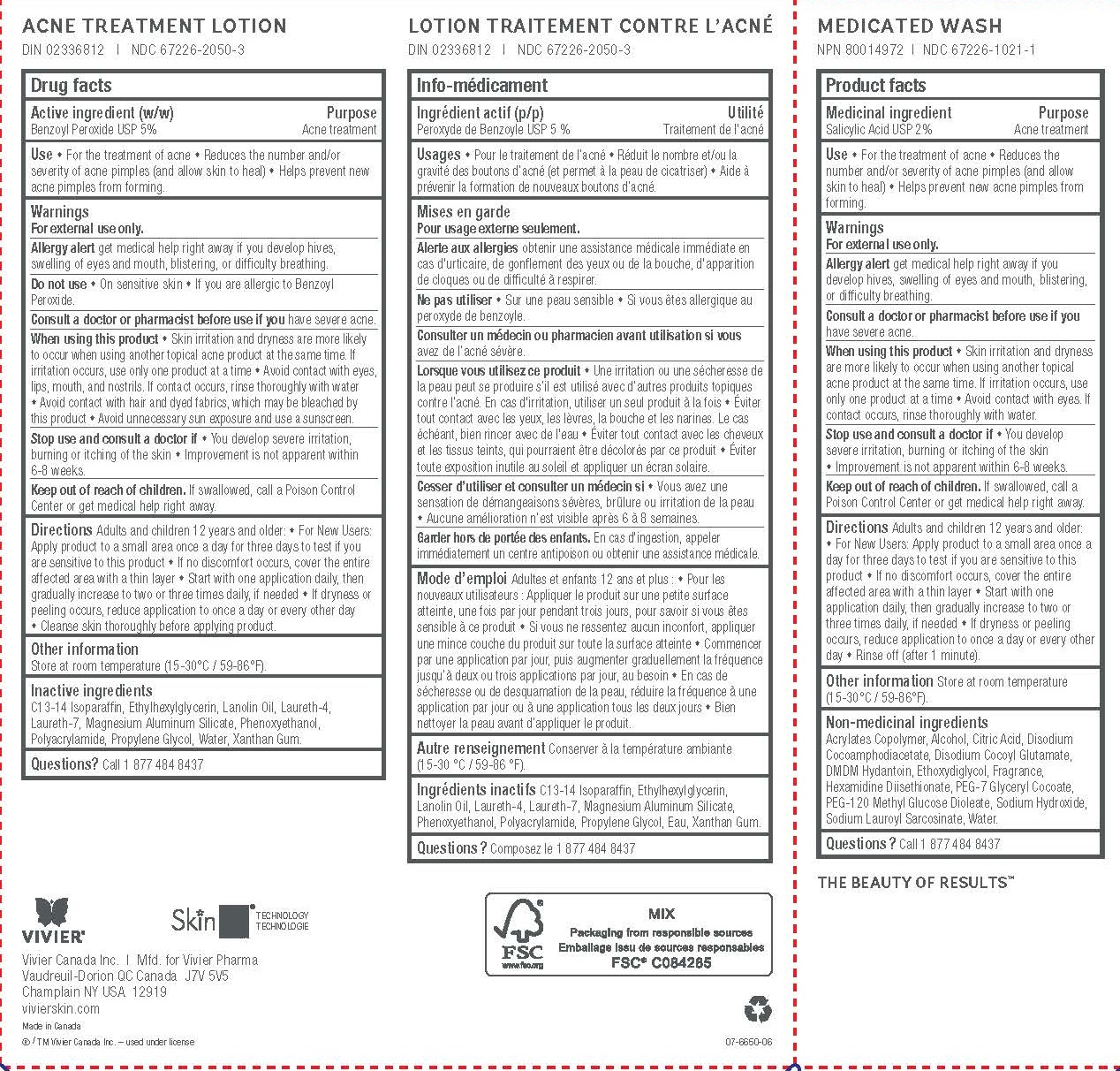 DRUG LABEL: Acne Treatment System
NDC: 67226-3026 | Form: KIT | Route: TOPICAL
Manufacturer: Vivier Pharma, Inc.
Category: otc | Type: HUMAN OTC DRUG LABEL
Date: 20231027

ACTIVE INGREDIENTS: BENZOYL PEROXIDE 50 mg/1 mL; SALICYLIC ACID 20 mg/1 mL
INACTIVE INGREDIENTS: C13-14 ISOPARAFFIN; ETHYLHEXYLGLYCERIN; LANOLIN OIL; LAURETH-4; LAURETH-7; MAGNESIUM ALUMINUM SILICATE; PHENOXYETHANOL; PROPYLENE GLYCOL; WATER; XANTHAN GUM; BUTYL ACRYLATE/METHYL METHACRYLATE/METHACRYLIC ACID COPOLYMER (18000 MW); ALCOHOL; CITRIC ACID MONOHYDRATE; DISODIUM COCOAMPHODIACETATE; DISODIUM COCOYL GLUTAMATE; DMDM HYDANTOIN; DIETHYLENE GLYCOL MONOETHYL ETHER; HEXAMIDINE DIISETHIONATE; PEG-7 GLYCERYL COCOATE; PEG-120 METHYL GLUCOSE DIOLEATE; SODIUM HYDROXIDE; SODIUM LAUROYL SARCOSINATE; WATER

Acne Treatment System

Active ingredient

Salicylic Acid USP 2%

Purpose

Acne treatment

Use

For the treatment of acne. Dries, clears and helps keep skin clear of new acne pimples, blackheads and whiteheads.

Warnings

For external use only.

Ask a doctor before use if you are

using other topical acne medications at the same time or immediately following use of this product may increase dryness or irritation of the skin. If this occurs, only one medication should be used unless directed by a doctor.

When using this product

do not get into eyes.

Stop use and ask a doctor if

excessive skin irritation develops or increases.

Keep out of reach of children.

If swallowed, get medical help or contact Poison Control Center right away.

Directions

• Wet face using lukewarm water. • Gently massage over face using fingertips. • Rinse completely. • Use both morning and night or as directed by a physician. • If dryness or peeling occurs, reduce application to once a day or every other day.

Other information

Store at room temperature (15-30°C / 59-86°F).

Inactive ingredients

Acrylates Copolymer, Alcohol, Citric Acid, Disodium Cocoamphodiacetate, Disodium Cocoyl Glutamate, DMDM Hydantoin, Ethoxydiglycol, Fragrance, Hexamidine Diisethionate, PEG-7 Glyceryl Cocoate, PEG-120 Methyl Glucose Dioleate, Sodium Hydroxide, Sodium Lauroyl Sarcosinate, Water/Eau.

Questions?

450 455 9779 1 877 484 8437